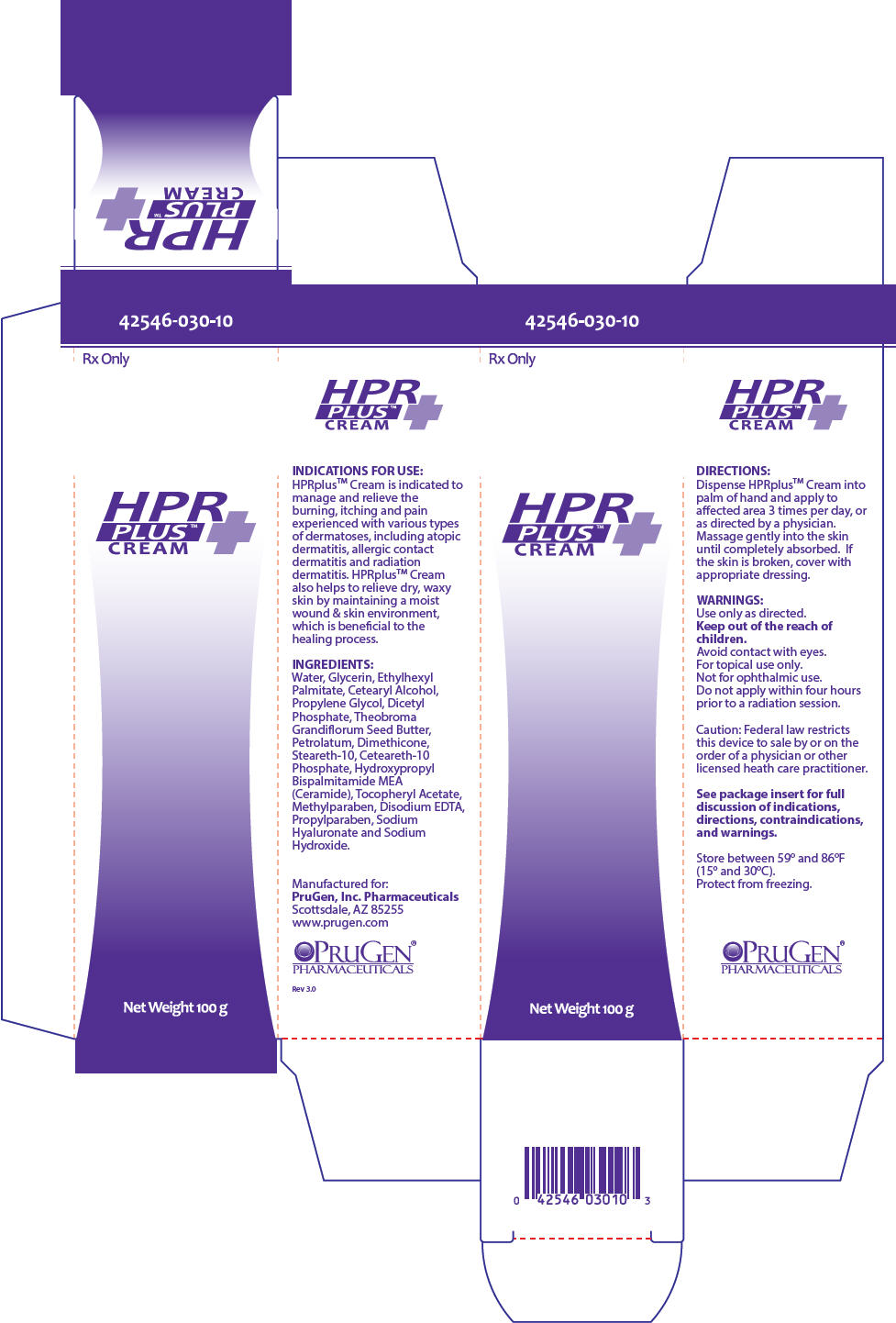 DRUG LABEL: HPRplus cream
NDC: 42546-030
Manufacturer: PruGen, Inc.
Category: other | Type: PRESCRIPTION MEDICAL DEVICE LABEL
Date: 20180706

HPRplus cream

INDICATIONS FOR USE

HPRplus is indicated to manage and relieve the burning, itching and pain experienced with various types of dermatoses, including atopic dermatitis, allergic contact dermatitis and radiation dermatitis. HPRplus also helps to relieve dry, waxy skin by maintaining a moist wound & skin environment, which is beneficial to the healing process.

CONTRAINDICATIONS

HPRplus is contraindicated in persons with a known hypersensitivity to any of the components of the formulation.

WARNINGS

Use only as directed.

Keep out of the reach of children.

Avoid contact with eyes.

For topical use only.

Not for ophthalmic use.

Do not apply within four hours prior to a radiation session.

HPRplus Emollient Foam:

Contents under pressure.

Do not puncture or incinerate container.

Do not expose to temperatures above 120oF (49oC).

PRECAUTIONS AND OBSERVATIONS

• HPRplus does not contain a sunscreen and should not be used prior to extended exposure to the sun.

• If clinical signs of infection are present, appropriate treatment should be initiated; use of HPRplus may be continued during the anti-infective therapy.

• If the condition does not improve within 10-14 days, consult a physician.

• HPRplus may dissolve fuchsin when this dye is used to define the margins of the radiation fields to be treated.

DIRECTIONS-CREAM:

Dispense HPRplus Cream into palm of hand and apply to affected area 3 times per day, or as directed by a physician. Massage gently into the skin until completely absorbed. If the skin is broken, cover with appropriate dressing.

DIRECTIONS-EMOLLIENT FOAM:

Important: Prime Can Before Initial Use.

To Prime Can: Shake can vigorously (until product moves inside can). Firmly strike bottom of can onto palm of other hand or a hard surface at least 3 times. Hold the can upright and direct initial spray to a non-skin surface. Until foam dispenses, DO NOT spray directly on the skin as the initial spray may expel cold liquid propellant. Press down on actuator for 1-3 seconds until foam begins to dispense. If foam does not dispense within 3 seconds, prime can again.

Before Each Use: Shake can vigorously. Firmly strike bottom of can onto palm of other hand or a hard surface at least 3 times.

During Use: Holding can upright, dispense HPRplus Emollient Foam into palm of hand and apply to affected area 3 times per day, or as directed by a physician. Massage gently into the skin until completely absorbed. If the skin is broken, cover with appropriate dressing. Wipe off any excess foam from actuator after use.

INGREDIENTS

Water, Glycerin, Ethylhexyl Palmitate, Cetearyl Alcohol, Propylene Glycol, Dicetyl Phosphate, Theobroma Grandiflorum Seed Butter, Petrolatum, Dimethicone, Steareth-10, Ceteareth-10 Phosphate, Hydroxypropyl Bispalmitamide MEA (Ceramide), Tocopheryl Acetate, Methylparaben, Disodium EDTA, Propylparaben, Sodium Hyaluronate and Sodium Hydroxide. HPRplus Emollient Foam also contains Hydrofluorocarbon 134a (propellant).

HOW SUPPLIED

HPRplus Cream is available in 100 g tubes (NDC 42546-030-10) and 450 g jars (NDC 42546-030-45).

HPRplus Emollient Foam is available in 100 g (NDC 42546-025-10) and 150 g (NDC 42546-025-15) canisters.

HPRplus Emollient Foam will not dispense entire contents. Container is overfilled to guarantee dispensing at least the listed amount.

Caution: Federal law restricts this device to sale by or on the order of a physician or other licensed heath care practitioner.

Store between 59o and 86oF (15o and 30oC). Protect from freezing.

HPRplus Emollient Foam: Store upright.

Manufactured for:

PruGen, Inc. Pharmaceuticals

Scottsdale, AZ 85255

www.prugen.com

PRINCIPAL DISPLAY PANEL - 100 g Tube Box

42546-030-10

Rx Only

HPR
PLUS™
CREAM

Net Weight 100 g